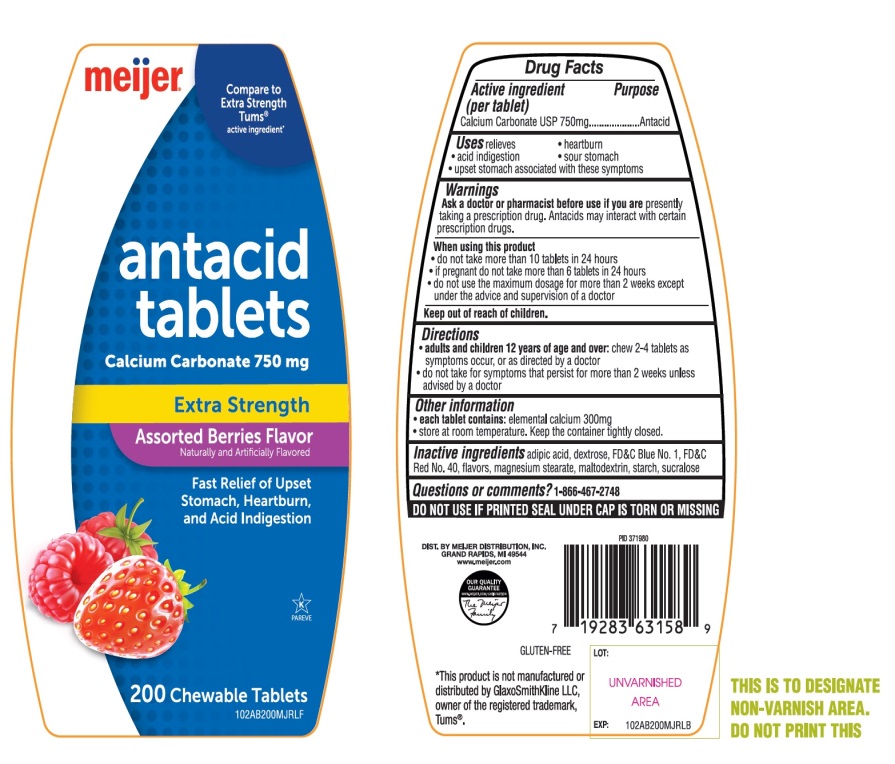 DRUG LABEL: meijer Extra Strength Antacid

NDC: 41250-232 | Form: TABLET, CHEWABLE
Manufacturer: MEIJER DISTRIBUTION INC
Category: otc | Type: HUMAN OTC DRUG LABEL
Date: 20251024

ACTIVE INGREDIENTS: CALCIUM CARBONATE 750 mg/1 1
INACTIVE INGREDIENTS: ADIPIC ACID; DEXTROSE, UNSPECIFIED FORM; FD&C BLUE NO. 1; FD&C RED NO. 40; MAGNESIUM STEARATE; MALTODEXTRIN; STARCH, CORN; SUCRALOSE

meijer®Extra Strength Antacid Calcium Carbonate Chewable Tablets

Active ingredient (per tablet)

Calcium Carbonate USP 750mg

Purpose

Antacid

Uses

relieves

• heartburn

• acid indigestion

• sour stomach

• upset stomach associated with these symptoms

Warnings

Ask a doctor or pharmacist before use if you arepresently taking a prescription drug. Antacids may interact with certain prescription drugs.

When using this product

- do not take more than 10 tablets in 24 hours
- If pregnant do not take more than 6 tablets in 24 hours
- do not use the maximum dosage for more than 2 weeks except under the advice and supervision of a doctor

Directions

- adults and children 12 years of age and over:chew 2-4 tablets as symptoms occur, or as directed by a doctor
- do not take for symptoms that persist for more than 2 weeks unless advised by a doctor

Other information

• each tablet contains: elemental calcium 300mg

• store at room temperature. Keep the container tightly closed.

Inactive ingredients

adipic acid, dextrose, FD&C Blue No. 1, FD&C Red No. 40, flavors, magnesium stearate, maltodextrin, starch, sucralose,

Questions or comments?

1-866-467-2748

SAFETY SEALED: DO NOT USE IF PRINTED SEAL UNDER CAP IS TORN OR MISSING

Package/Label Principal Display Panel

meijer®

NDC 41250-232-20

Compare to Extra Strength Tums® active ingredient*

antacid tablets

Calcium Carbonate 750 mg

Extra Strength

Assorted Berries Flavor

Naturally and Artificially Flavored

Fast Relief of Upset Stomach, Heartburn, and Acid indigestion

200 Chewable Tablets

GLUTEN-FREE

OUR QUALITY GUARANTEE

www.meijer.com/Satisfaction

DIST. BY MEIJER DISTRIBUTION, INC.

GRAND RAPIDS, MI 49544

www.meijer.com

*This product is not manufactured or distributed by GlaxoSmithKline LLC, owner of the registered trademark, Tums®.